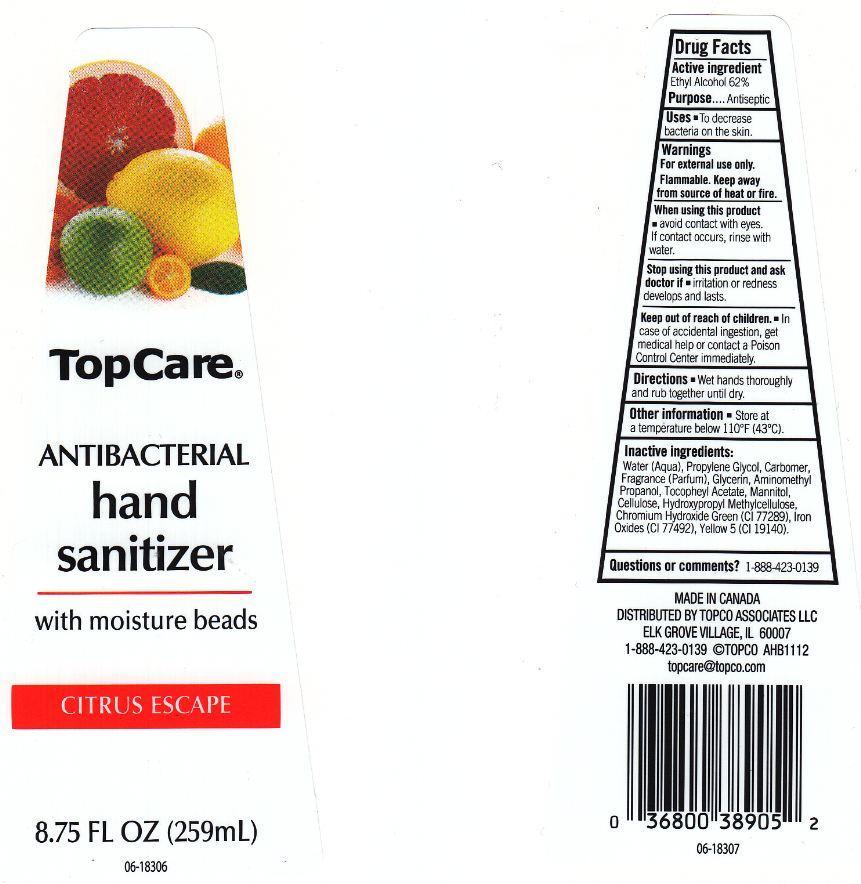 DRUG LABEL: TOPCARE
NDC: 36800-258 | Form: LIQUID
Manufacturer: TOPCO ASSOCIATES LLC
Category: otc | Type: HUMAN OTC DRUG LABEL
Date: 20130321

ACTIVE INGREDIENTS: ALCOHOL 620 mg/1 mL
INACTIVE INGREDIENTS: WATER; PROPYLENE GLYCOL; CARBOMER 934; GLYCERIN; AMINOMETHYLPROPANOL; .ALPHA.-TOCOPHEROL ACETATE; MANNITOL; POWDERED CELLULOSE; HYPROMELLOSES; CHROMIUM HYDROXIDE GREEN; FERRIC OXIDE YELLOW; FD&C YELLOW NO. 5

DRUG FACTS

ACTIVE INGREDIENT

ETHYL ALCOHOL 62%

PURPOSE

ANTISEPTIC

USES

TO DECREASE BACTERIA ON THE SKIN.

WARNINGS

FOR EXTERNAL USE ONLY. FLAMMABLE. KEEP AWAY FROM SOURCE OF HEAT OR FIRE.

WHEN USING THIS PRODUCT

AVOID CONTACT WITH EYES. IF CONTACT OCCURS, RINSE WITH WATER.

STOP USING THIS PRODUCT AND ASK DOCTOR IF

IRRITATION OR REDNESS DEVELOPS AND LASTS.

KEEP OUT OF REACH OF CHILDREN

IN CASE OF ACCIDENTAL INGESTION, GET MEDICAL HELP OR CONTACT A POISON CONTROL CENTER IMMEDIATELY.

DIRECTIONS

WET HANDS THOROUGHLY AND RUB TOGETHER UNTIL DRY.

OTHER INFORMATION

STORE AT A TEMPERATURE BELOW 110F (43C).

INACTIVE INGREDIENTS:

WATER (AQUA), PROPYLENE GLYCOL, CARBOMER, FRAGRANCE (PARFUM), GLYCERIN, AMINOMETHYL PROPANOL, TOCOPHERYL ACETATE, MANNITOL, CELLULOSE, HYDROXYPROPYL METHYLCELLULOSE, CHROMIUM HYDROXIDE GREEN (CI 77289), IRON OXIDES (CI 77492), YELLOW 5 (CI 19140).

QUESTIONS OR COMMENTS?

1-888-423-0139